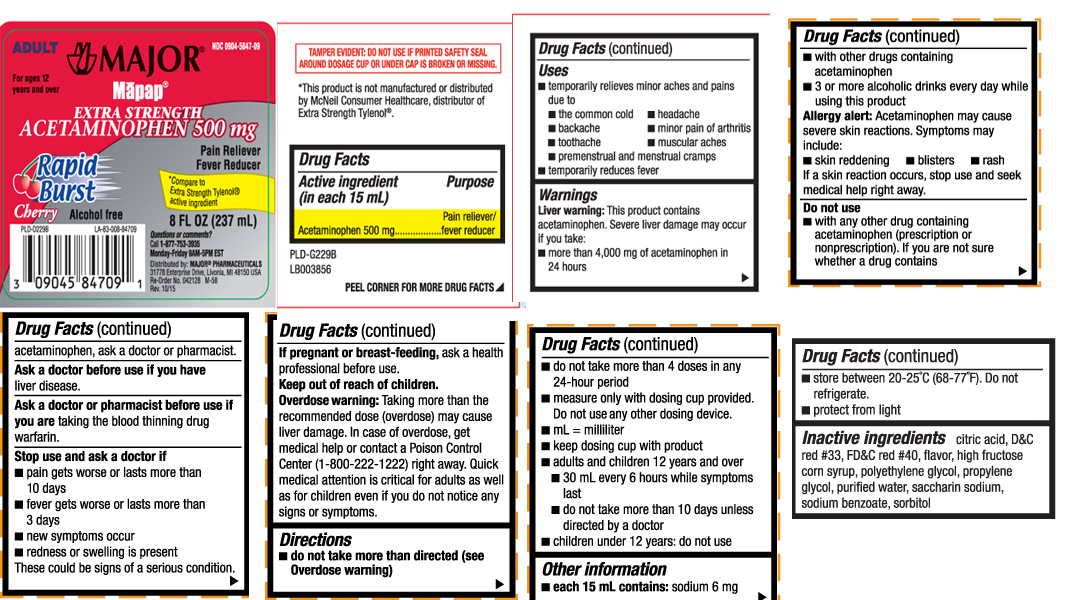 DRUG LABEL: Extra Strength Acetaminohpen
NDC: 0904-5847 | Form: LIQUID
Manufacturer: Major Pharmaceuticals
Category: otc | Type: HUMAN OTC DRUG LABEL
Date: 20240827

ACTIVE INGREDIENTS: ACETAMINOPHEN 500 mg/15 mL
INACTIVE INGREDIENTS: CITRIC ACID MONOHYDRATE; HIGH FRUCTOSE CORN SYRUP; POLYETHYLENE GLYCOL 300; PROPYLENE GLYCOL; WATER; D&C RED NO. 33; FD&C RED NO. 40; SACCHARIN SODIUM ANHYDROUS; SODIUM BENZOATE; SORBITOL

Drug Facts

Active Ingredients (in each 15 mL)

Acetaminophen 500 mg

Purpose

Pain reliever/Fever reducer

Uses

- temporarily relieves minor aches and pains due to
  - the common cold
  - headache
  - backache
  - minor pain of arthritis
  - toothache
  - muscular aches
  - premenstrual and menstrual cramps
- temporarily reduces fever

Warnings

Liver warning: This product contains acetaminophen. Severe liver damage may occur if you take:

- more than 4000 mg of acetaminophen in 24 hours
- with other drugs containing acetaminophen
- 3 or more alcoholic drinks every day while using this product

Allergy alert: Acetaminophen may cause severe skin reactions.Symptoms may include:

- skin reddening
- blisters
- rash

If a skin reaction occurs, stop use and seek medical help right away.

Do Not Use

- with any other drug containing acetaminophen (prescription or non-prescription). If you are not sure whether a drug contains
  acetaminophen, ask a doctor or pharmacist

Ask a doctor before use if you have

liver disease

Ask a doctor or pharmacist before use if you are

taking the blood thinning drug warfarin

Stop use and ask a doctor if

• pain gets worse or lasts for more than 10 days
• fever gets worse or lasts for more than 3 days
• new symptoms occur
• redness or swelling is present
These could be signs of a serious condition.

If pregnant or breast-feeding

ask a health professional before use.

Keep out of reach of children.

Overdose warning: Taking more than the recommended dose (overdose) may cause liver damage. In case of accidental overdose, seek professional assistance or contact a Poison Control Center (1-800-222-1222) right away.Quick medical attention is critical for adults as well as for children even if you do not notice any signs or symptoms.

Directions

- do not take more than directed (see overdose warning)
- do not take more than 4 doses in any 24 hour period
- measure only with dosing cup provided. Do not use any other dosing device
- mL=milliliter
- keep dosing cup with product
- adults and children 12 years and over
  - 30 mL every 6 hours while symptoms last
  - do not take more than 10 days unless directed by a doctor
- children under 12 years: do not use

Other Information

- each 15 mL contains: sodium 6 mg
- store between 20-25ºC (68-77ºF). Do not refrigerate
- protect from light

Inactive Ingredients

citric acid, D&C red #33, FD&C red #40, flavor, high fructose corn syrup, polyethylene glycol, propylene glycol, purified water, saccharin sodium, sodium benzoate, sorbitol

Principal Display Panel

Major Mapap

ADULT

For ages 12 years and over

Extra Strength Actetaminophen 500 mg

Rapid Burst Cherry

Pain reliever

fever reducer

*COmpare to Extra strength Tylenol® active ingredient

Alcohol free

FL OZ (mL)

Questions or comments?
Call 1-877-753-3935

Monday-Fridat 9AM-5PM EST

Distributed by: MAjor Pharmaceuticals

17177 N Laurel Park Drive, Suite 233

Livonia, MI 48152 USA

TAMPER EVIDENT: DO NOT USE IF PRINTED SAFETY SEAL AROUND DOSAGE CUP OR UNDER CAP IS BROKEN OR MISSSING.

*This product is not manufactured or distributed by McNeil Consumer Healthcare, distributor of Extra Strength Tylenol®

Package label

Major MAPAP